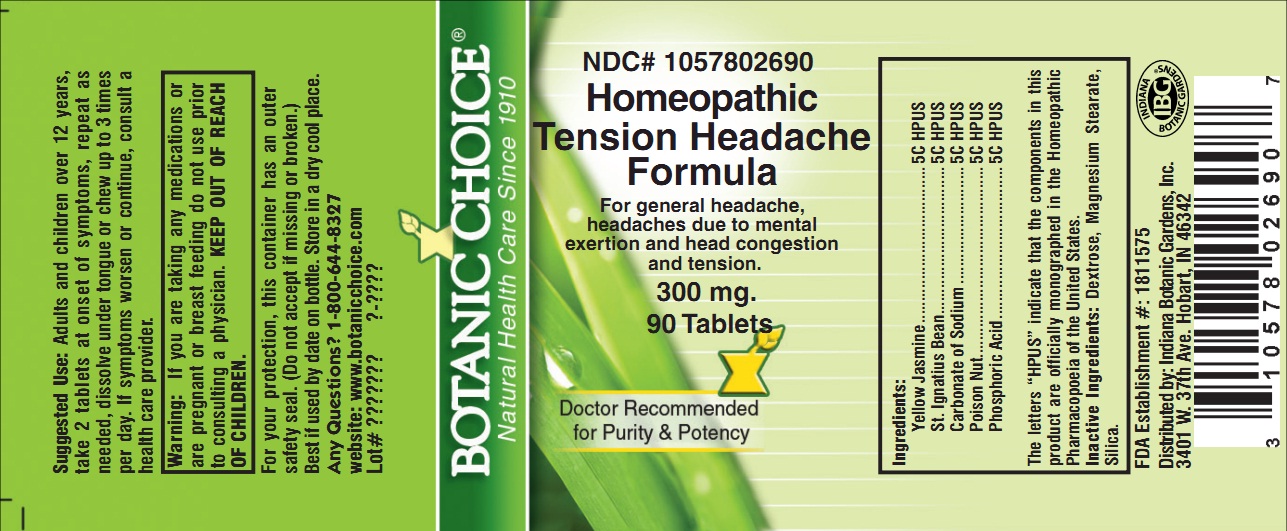 DRUG LABEL: Homeopathic Tension Headache Formula
NDC: 10578-026 | Form: TABLET
Manufacturer: Indiana Botanic Gardens
Category: homeopathic | Type: HUMAN OTC DRUG LABEL
Date: 20120630

ACTIVE INGREDIENTS: GELSEMIUM SEMPERVIRENS ROOT 5 [hp_C]/1 1; STRYCHNOS IGNATII SEED 5 [hp_C]/1 1; SODIUM CARBONATE 5 [hp_C]/1 1; STRYCHNOS NUX-VOMICA SEED 5 [hp_C]/1 1; PHOSPHORIC ACID 5 [hp_C]/1 1
INACTIVE INGREDIENTS: DEXTROSE; MAGNESIUM STEARATE; SILICON DIOXIDE

Homeopathic Tension Headache Formula

Suggested Use:

Adults and children over 12 years, take 2 tablets at onset of symptoms, repeat as needed, dissolve under tongue or chew up to 3 times per day.

STOP USE

If symptoms worsen or continue, consult a health care provider.

Warning:

If you are taking any medications or are pregnant or breast feeding do not use prior to consulting a physician.

KEEP OUT OF REACH OF CHILDREN.

For your protection, this container has an outer safety seal. (Do not accept if missing or broken.) Best if used by date on bottle. Store in a dry cool place.

Any Questions?

Any Questions? 1-800-644-8327

website: www.botanicchoice.com

PURPOSE

INDICATIONS AND USAGE

For general headache, headaches due to mental exertion and head congestion and tension.

Ingredients:

Yellow Jasmine .................................... 5C HPUS

St. Ignatius Bean .................................. 5C HPUS

Carbonate of Sodium ........................... 5C HPUS

Poison Nut............................................ 5C HPUS

Phosphoric Acid ................................... 5C HPUS

The letters “HPUS” indicate that the components in this product are officially monographed in the Homeopathic Pharmacopoeia of the United States.

Inactive Ingredients:

Dextrose, Magnesium Stearate, Silica.

FDA Establishment #: 1811575

Distributed by: Indiana Botanic Gardens, Inc.

3401 W. 37th Ave. Hobart, IN 46342

Botanic Choice®

Natural Health Care Since 1910

NDC# 1057802690

Homeopathic Tension Headache Formula

For general headache, headaches due to mental exertion and head congestion and tension.

300 mg.

90 Tablets

Doctor Recommended for Purity & Potency